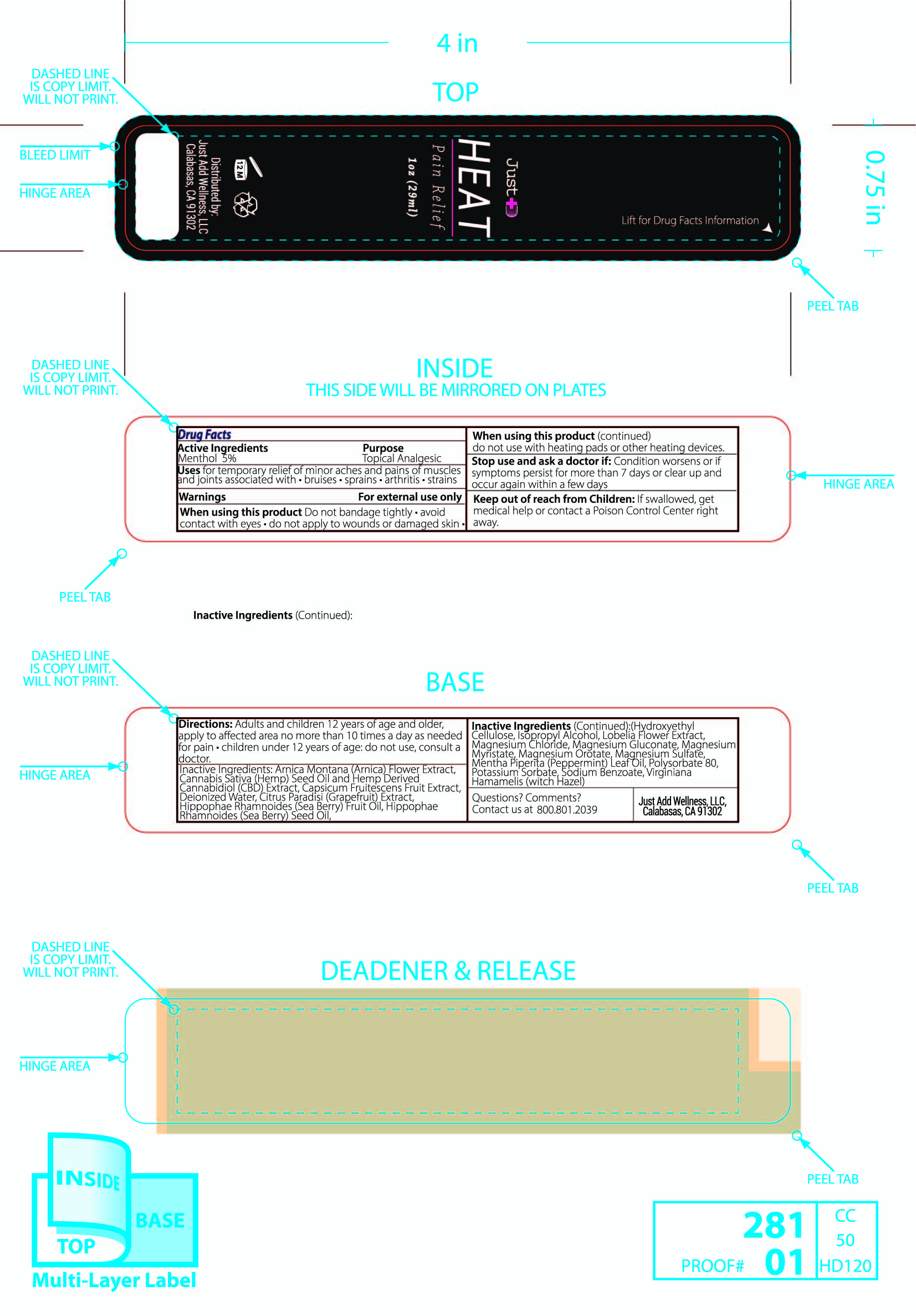 DRUG LABEL: Just ADD HEAT Pain Relief
NDC: 76348-695 | Form: LIQUID
Manufacturer: RENU LABORATORIES, INC.
Category: otc | Type: HUMAN OTC DRUG LABEL
Date: 20210921

ACTIVE INGREDIENTS: MENTHOL 1.4 g/28 g
INACTIVE INGREDIENTS: WATER; METHYLCELLULOSE (4000 CPS); PEPPERMINT OIL; ARNICA MONTANA; SODIUM BENZOATE; POTASSIUM SORBATE; MAGNESIUM MYRISTATE; WITCH HAZEL; CANNABIS SATIVA SEED OIL; MAGNESIUM OROTATE; LOBELIA INFLATA LEAF; MAGNESIUM GLUCONATE; MAGNESIUM CHLORIDE; POLYSORBATE 80; HIPPOPHAE RHAMNOIDES SEED OIL; ISOPROPYL ALCOHOL; CANNABIDIOL; MAGNESIUM SULFATE, UNSPECIFIED; HIPPOPHAE RHAMNOIDES FRUIT OIL; TABASCO PEPPER

JUST ADD HEAT Pain Relief

ACTIVE INGREDIENT

Menthol 5 percent

PURPOSE

Topical Analgesic

Uses

for temporary relief of minor aches and pains of muscles and joints associated with

- bruises
- sprains
- arthritis
- strains

WARNINGS

For external use only

WHEN USING

Do not bandage tightly

Avoid contact with eyes

Do not apply to wounds or damaged skin

Do not use with heating pads or other heating devices

Stop use and ask a doctor if

Condition worsens or if symptoms persist for more than 7 days or clear up and occur again within a few days

KEEP OUT OF REACH OF CHILDREN

If swallowed, get medical help or contact a Poison Control Center right away.

DOSAGE AND ADMINISTRATION

Adults and children twelve years of age and older,

apply to affected area no more than ten times a day as needed for pain

children under twelve years of age do not use, consult a doctor

INACTIVE INGREDIENT

Arnica Montana (Arnica) Flower Extract, Cannabis Sativa (Hemp) Seed Oil and Hemp Derived Cannabidiol (CBD) Extract, Capsicum Frutescens (Pepper) Fruit Extract, Deionized Water, Citrus Paradisi (Grapefruit) Extract, Hippophae Rhamnoides (Sea Berry) Fruit Oil, Hippophae Rhamnoides (Sea Berry) Seed Oil, Hydroxyethyl Cellulose, Isopropyl Alcohol, Lobelia Flower Extract, Magnesium Chloride, Magnesium Gluconate, Magnesium Myristate, Magnesium Orotate, Magnesium Sulfate, Menth Piperita (Peppermint) Leaf Oil, Polysorbate 80, Potassium Sorbate, Sodium Benzoate, Hamamelis Virginiana (Witch Hazel)

Questions? Comments ?

Contact us at 800.801.2039

Just Add Wellness, LLC

Calabasas, CA 91302

JUST ADD HEAT PRODUCT LABEL